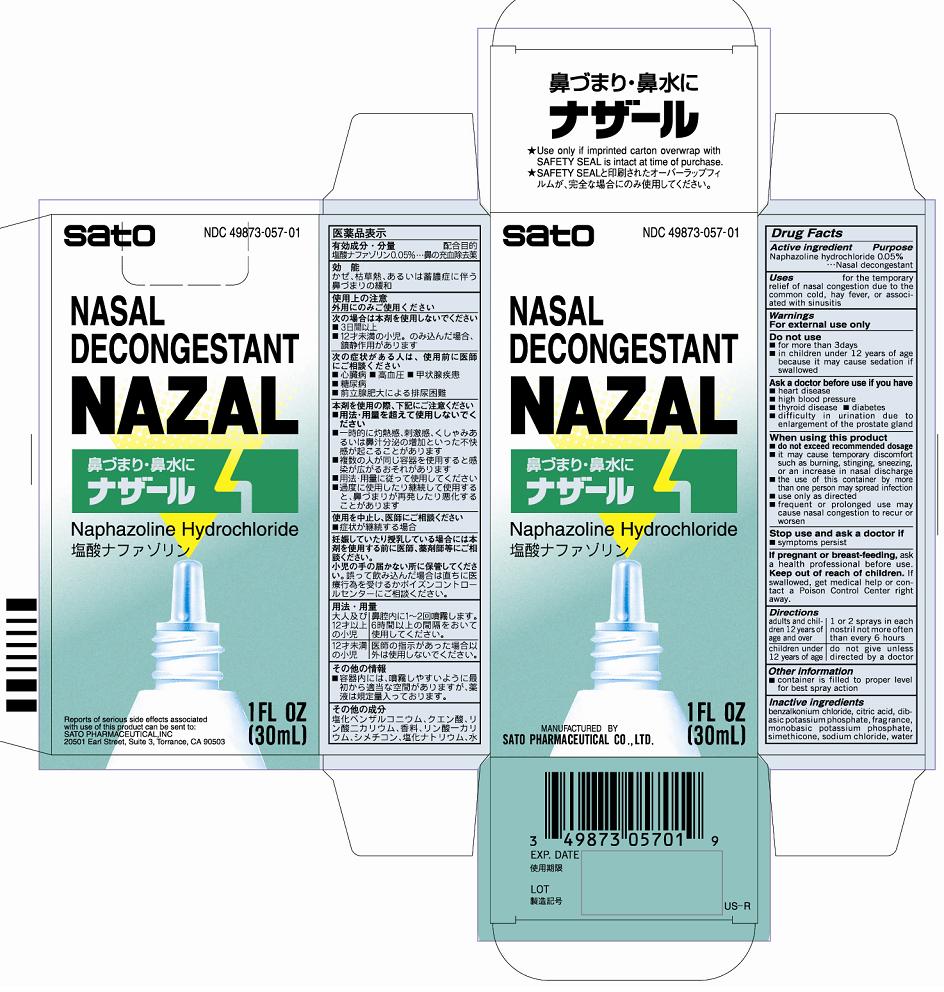 DRUG LABEL: Nazal
NDC: 49873-057 | Form: LIQUID
Manufacturer: Sato Pharmaceutical Co., Ltd.
Category: otc | Type: HUMAN OTC DRUG LABEL
Date: 20231206

ACTIVE INGREDIENTS: NAPHAZOLINE HYDROCHLORIDE 50 mg/100 mL
INACTIVE INGREDIENTS: CITRIC ACID MONOHYDRATE; POTASSIUM PHOSPHATE, DIBASIC; POTASSIUM PHOSPHATE, MONOBASIC; DIMETHICONE; SILICON DIOXIDE; SODIUM CHLORIDE; WATER; BENZALKONIUM CHLORIDE

Nazal

Active ingredients
Naphazoline hydrochloride 0.05%

Purpose Nasal decongestant

INDICATIONS AND USAGE

Uses for the temporary relief of nasal congestion due to the common cold, hay fever, or associated with sinusitis

Warnings
For external use only

Do not use
■for more than 3 days
■in children under 12 years of age because it may cause sedation if swallowed

Ask a doctor before use if you have
■heart disease
■high blood pressure
■thyroid disease ■diabetes
■difficulty in urination due to enlargement of the prostate gland

When using this product
■do not exceed recommended dosage
■if may cause temporary discomfort such as burning, stinging, sneezing, or an increase in nasal discharge
■the use of this container by more than one person may spread infection
■use only as directed
■frequent or prolonged use may cause nasal congestion to recur or worsen

Stop use and ask a doctor if
■symptoms persist

PREGNANCY OR BREAST FEEDING

If pregnant or breast-feeding, ask a health professional before use.

KEEP OUT OF REACH OF CHILDREN

Keep our of reach of children. In case of accidental overdose, get medical help or contact a Poison Control Center right away.

Directions
Adults and children 12 years of age and older - 1 or 2 sprays in each nostril not more often than every 6 hours
Children under 12 years of age - do not give unless directed by a doctor

Other information
■container is filled to proper level for best spray action

Inactive ingredients
benzalkonium chloride, citric acid, dibasic potassium phosphate, fragrance, monobasic potassium phosphate, simethicone, sodium chloride, water

PACKAGE LABEL

nazalcart.jpg